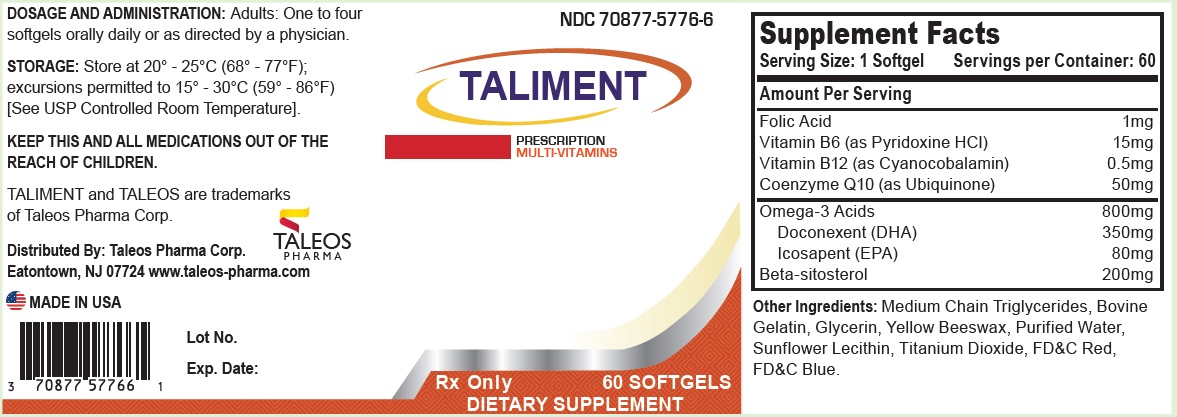 DRUG LABEL: TALIMENT
NDC: 70877-5776 | Form: CAPSULE, COATED
Manufacturer: Taleos Pharma
Category: other | Type: DIETARY SUPPLEMENT
Date: 20180406

ACTIVE INGREDIENTS: FOLIC ACID 1 mg/1 1; PYRIDOXINE HYDROCHLORIDE 15 mg/1 1; CYANOCOBALAMIN 0.5 mg/1 1; UBIDECARENONE 50 mg/1 1; OMEGA-3 FATTY ACIDS 800 mg/1 1; DOCONEXENT 350 mg/1 1; ICOSAPENT 80 mg/1 1; .BETA.-SITOSTEROL 200 mg/1 1
INACTIVE INGREDIENTS: MEDIUM-CHAIN TRIGLYCERIDES; GLYCERIN; YELLOW WAX; WATER; LECITHIN, SUNFLOWER; TITANIUM DIOXIDE

TALIMENT Softgels

HEALTH CLAIM

Rx Only

DESCRIPTION

TALIMENT is a prescription multi-vitamin in the form of a red, oblong softgel.

INDICATION AND USAGE

TALIMENT is a prescription multi-vitamin supplement with DHA and EPA that can be taken to improve nutritional status in conditions requiring Essential Fatty Acid, Vitamin B12 and B6 and Folic Acid supplementation capsule.

CONTRAINDICATIONS

This product is contraindicated in patients with a known hypersensitivity to any of the ingredients.

WARNING

Folic Acid in doses above 0.1 mg daily may obscure pernicious anemia in that hematological remission can occur while neurological manifestations remain progressive. Folic Acid alone is improper therapy in the treatment of pernicious anemia and other megaloblastic anemias where vitamin B12 is deficient.

Ingestion of more than 3 grams of omega-3 fatty acids per day has been shown to have potential antithrombotic effects, including increased bleeding time and INR. Administration of omega-3 fatty acids should be avoided in patients on anticoagulants and in those known to have an inherited or acquired bleeding diathesis.

KEEP THIS AND ALL MEDICATIONS OUT OF THE REACH OF CHILDREN.

PRECAUTIONS

Folic Acid in doses above 0.1 mg daily may obscure pernicious anemia in that hematological remission can occur while neurological manifestations remain progressive.

ADVERSE REACTIONS

Allergic sensitization has been reported following both oral and parenteral administration of folic acid.

DOSAGE AND ADMINISTRATION

Adults: One to four softgels orally daily or as directed by a physician.

Supplement Facts
Serving Size: 1 Softgel | Servings per Container: 60
Amount Per Serving
Folic Acid |  | 1mg
Vitamin B6 (as Pyridoxine HCl) |  | 15mg
Vitamin B12 (as Cyanocobalamin) |  | 0.5mg
Coenzyme Q10 (as Ubiquinone) |  | 50mg
Omega-3 Acids |  | 800mg
Doconexent (DHA) |  | 350mg
Icosapent (EPA) |  | 80mg
Beta-sitosterol |  | 200mg

STORAGE

Store at 20° - 25°C (68° - 77°F); excursions permitted to 15° - 30°C (59° - 86°F) [See USP Controlled Room Temperature.]

Dispense in a well-closed, tight, light-resistant container as defined by the USP using a child resistant closure.

HOW SUPPLIED

TALIMENT softgels are supplied as red oblong, softgels. TALIMENT softgels are available in bottles of 60 (NDC: 70877-5776-6). Each tablet of TALIMENT contains 1 mg of Folic Acid , 15 mg of pyridoxine hydrochloride, 0.5 mg of cyanocobalamin, 50 mg of coenzyme Q10, 800 mg of omega-3 acids including 350 mg of Doconexent, 80 mg of Icosapent, and 200 mg of beta-sitosterol.

HEALTH CLAIM

Distributed By:
Taleos Pharma Corp.
Eatontown, NJ 07724
www.taleos-pharma.com

TALIMENT and TALEOS are trademarks of Taleos Pharma Corp.

PRINCIPAL DISPLAY PANEL - 60 Softgel Bottle Label

70877-5776-6

TALIMENT

PRESCRIPTION
MULTI-VITAMINS

Rx Only 60 SOFTGELS

DIETARY SUPPLEMENT